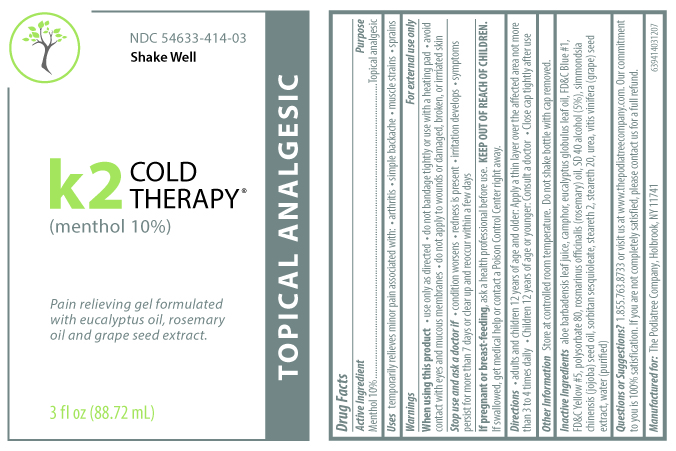 DRUG LABEL: K2 Cold Therapy
NDC: 54633-414 | Form: LIQUID
Manufacturer: The Podiatree Co
Category: otc | Type: HUMAN OTC DRUG LABEL
Date: 20260108

ACTIVE INGREDIENTS: MENTHOL 10 g/100 mL
INACTIVE INGREDIENTS: ALOE VERA LEAF; CAMPHOR (NATURAL); EUCALYPTUS GLOBULUS LEAF; FD&C BLUE NO. 1; FD&C YELLOW NO. 5; POLYSORBATE 80; ROSMARINUS OFFICINALIS WHOLE; ALCOHOL; SIMMONDSIA CHINENSIS WHOLE; SORBITAN SESQUIOLEATE; STEARETH-2; STEARETH-20; UREA; VITIS VINIFERA SEED; WATER

Active ingredient:

Menthol 10%

Purpose

Topical Analgesic

Uses

TEMPORARILY RELIEVES MINOR PAIN ASSOCIATED WITH:

- ARTHRITIS
- SIMPLE BACKACHE
- MUSCLE STRAINS
- SPRAINS

Warnings

For external use only.

When using this product

- Use only as directed
- Do not bandage tighlty or use with a heating pad
- Avoid contact with eyes and mucous membranes
- Do not apply to wounds or damaged, broken, or irritated skin.

Stop use and ask a doctor if

- Condition worsens
- Redness is present
- Irritation develops
- Symptoms persist for more than 7 days or clear up and reoccur within a few days

If pregnant or breast-feeding

ask a health professional before use.

Keep out of reach of children.

If swallowed, get medical help or contact a Poison Control Center right away.

Directions

- Adults and children 12 years of age and older: Apply a thin layer over the affected area not more than 3 to 4 times daily.
- Children 12 years of age or younger: Consult a doctor.
- Close cap tightly after use.

Other information

Store at controlled room temperature. Do not shake bottle with cap removed.

Inactive Ingredients

Aloe Barbadensis Leaf Juice, Camphor, Eucalyptus Globulus Leaf Oil, FD&C Blue #1, FD&C Yellow #5, Polysorbate 80, Rosmarinus Officinalis (Rosemary) Oil, SD 40 Alcohol (5%) Simmondsia Chinensis (Jojoba) Seed Oil, Sorbitan Sesquioleate, Steareth 2, Steareth 20, Urea, Vitis Vinifera (Grape) Seed Extract, Water (Purified)

Questions or Suggestions?

1.855.763.8733 or visit us at www.thepodiatreecompany.com. Our commitment to you is 100% satisf ication. If you are not completely satisfied, please contact us for a full refund.